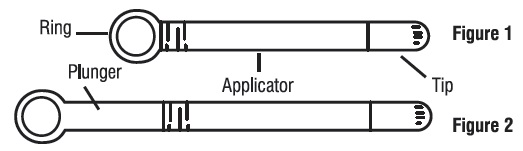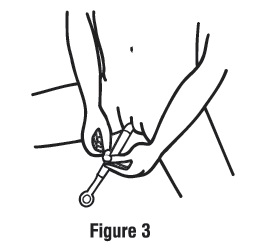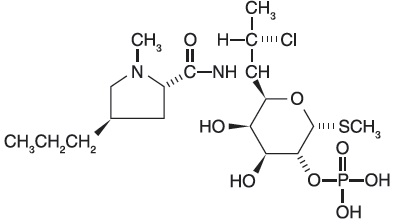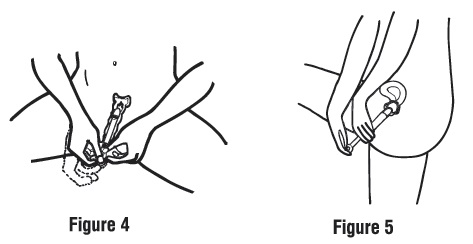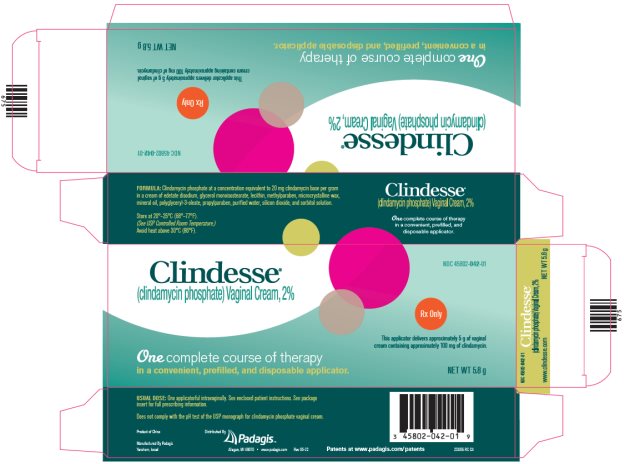 DRUG LABEL: Clindesse
NDC: 45802-042 | Form: CREAM
Manufacturer: Padagis Israel Pharmaceuticals Ltd
Category: prescription | Type: HUMAN PRESCRIPTION DRUG LABEL
Date: 20250130

ACTIVE INGREDIENTS: CLINDAMYCIN PHOSPHATE 100 mg/5 g
INACTIVE INGREDIENTS: EDETATE DISODIUM; GLYCERYL ISOSTEARATE; LECITHIN, SOYBEAN; METHYLPARABEN; MICROCRYSTALLINE WAX; MINERAL OIL; POLYGLYCERYL-3 OLEATE; PROPYLPARABEN; SILICON DIOXIDE; SORBITOL; WATER

HIGHLIGHTS OF PRESCRIBING INFORMATION

These highlights do not include all the information needed to use CLINDESSE safely and effectively. See full prescribing information for CLINDESSE.
CLINDESSE® (clindamycin phosphate) vaginal cream
Initial U.S. Approval: 1972

1 INDICATIONS AND USAGE

Clindesse is a lincosamide antibacterial indicated for the treatment of bacterial vaginosis in non-pregnant women (1.1)

2 DOSAGE AND ADMINISTRATION

- For intravaginal use only
- A single applicator of cream administered once intravaginally at any time of the day (2)
- Not for ophthalmic, dermal, or oral use

3 DOSAGE FORMS AND STRENGTHS

Vaginal cream: 2% clindamycin phosphate in one single-dose, pre-filled disposable applicator that delivers approximately 5 g of cream containing approximately 100 mg of clindamycin (3)

4 CONTRAINDICATIONS

- History of hypersensitivity to clindamycin or other lincosamides (4.1)
- History of regional enteritis, ulcerative colitis, or a history of Clostridioides difficile-associated diarrhea (4.2, 5.1)

5 WARNINGS AND PRECAUTIONS

- Clostridioides difficile-Associated Diarrhea: Discontinue and evaluate if diarrhea occurs (5.1)
- Use with Condoms and Vaginal Contraceptive Diaphragms: The use of barrier contraceptives (condoms or vaginal contraceptive diaphragms) is not recommended concurrently or for 5 days following treatment. Condoms may not be reliable for preventing pregnancy or for protecting against transmission of HIV and other sexually transmitted diseases during this time period (5.2, 8.3)

6 ADVERSE REACTIONS

Most common adverse reactions reported in ≥2% of patients and at a higher rate in the Clindesse group than in the placebo group are vaginosis fungal (14%), headache (7%), back pain (5%), constipation (2%), and urinary tract infection (2%) (6.1)

To report SUSPECTED ADVERSE REACTIONS, contact Padagis® at 1-866-634-9120 or FDA at 1-800-FDA-1088 or www.fda.gov/medwatch.

7 DRUG INTERACTIONS

Neuromuscular blocking agents: Enhanced action of neuromuscular blocking agents can occur; use with caution (7.1)

FULL PRESCRIBING INFORMATION

1 INDICATIONS AND USAGE

1.1 Treatment of Bacterial Vaginosis

Clindesse is indicated for the treatment of bacterial vaginosis (formerly referred to as Haemophilus vaginitis, Gardnerella vaginitis, nonspecific vaginitis, Corynebacterium vaginitis, or anaerobic vaginosis) in non-pregnant women.

2 DOSAGE AND ADMINISTRATION

The recommended dose is the complete contents of a single pre-filled applicator containing 5 g of Clindesse cream administered once intravaginally at any time of the day.

Not for ophthalmic, dermal, or oral use.

3 DOSAGE FORMS AND STRENGTHS

Clindesse is an intravaginal cream containing clindamycin phosphate 2%. Each pre-filled, single-dose applicator delivers approximately 5 g of cream containing approximately 100 mg of clindamycin.

4 CONTRAINDICATIONS

4.1 Hypersensitivity

Clindesse is contraindicated in individuals with a history of hypersensitivity to clindamycin or other lincosamides. Reported reactions to other formulations of clindamycin include rashes, urticaria, erythema multiforme, and anaphylactoid reactions [see Adverse Reactions (6.2)].

4.2 History of Bowel Disease

Clindesse is contraindicated in patients with regional enteritis, ulcerative colitis, or a history of Clostridioides difficile-associated diarrhea.

5 WARNINGS AND PRECAUTIONS

5.1 Clostridioides difficile-Associated Diarrhea (CDAD)

Clostridioides difficile-associated diarrhea (CDAD) has been reported with use of nearly all antibacterial agents, including clindamycin, and may range in severity from mild diarrhea to fatal colitis. Treatment with antibacterial agents alters the normal flora of the colon leading to overgrowth of C. difficile.

C. difficile produces toxins A and B which contribute to the development of CDAD. Hypertoxin producing strains of C. difficile cause increased morbidity and mortality, as these infections can be refractory to antimicrobial therapy and may require colectomy. CDAD must be considered in all patients who present with diarrhea following antibiotic use. Careful medical history is necessary since CDAD has been reported to occur over two months after the administration of antibacterial agents.

If CDAD is suspected or confirmed, ongoing antibiotic use not directed against C. difficile may need to be discontinued. Appropriate fluid and electrolyte management, protein supplementation, antibiotic treatment of C. difficile, and surgical evaluation should be instituted as clinically indicated [see Adverse Reactions (6.2)].

5.2 Use with Condoms and Vaginal Contraceptive Diaphragms

This cream contains mineral oil that may weaken latex or rubber products such as condoms or vaginal contraceptive diaphragms. Therefore, the use of such barrier contraceptives is not recommended concurrently or for 5 days following treatment with Clindesse. During this time period, condoms may not be reliable for preventing pregnancy or for protecting against transmission of HIV and other sexually transmitted diseases [see Use in Specific Populations (8.3)].

6 ADVERSE REACTIONS

6.1 Clinical Study Experience

Because clinical trials are conducted under widely varying conditions, adverse reaction rates observed in the clinical trials of a drug cannot be directly compared to rates in the clinical trials of another drug and may not reflect the rates observed in practice.

The data described below reflect exposure to Clindesse in 368 patients. Clindesse was studied in three clinical studies: placebo-controlled (n=85), active-controlled (n=263), and single-arm (n=20). The population was female, aged 18 to 78, who were diagnosed with bacterial vaginosis. Patient demographics in the trials were 51% Caucasian, 36% Black, 10% Hispanic, and 3% Asian, other or unknown. All patients received 100 mg clindamycin phosphate cream intravaginally in a single dose.

Of the 368 women treated with a single dose of Clindesse, 1.6% of the patients discontinued therapy due to adverse reactions. Adverse reactions occurred in 126 of 368 patients (34%) treated with Clindesse and in 32 of 85 patients (38%) treated with placebo.

Adverse reactions occurring in ≥2% of patients receiving Clindesse in the placebo-controlled clinical trial are shown in Table 1.

Table 1. Adverse Reactions Occurring in ≥2% of Clindesse-Treated Patients and at a Higher Rate than Placebo-Treated Patients

Adverse Reactions | Clindesse N=85 n (%) | Placebo N=85 n (%)
Vaginosis fungal NOS* | 12 (14) | 7 (8)
Headache NOS | 6 (7) | 2 (2)
Back Pain | 4 (5) | 1 (1)
Constipation | 2 (2) | 0 (0)
Urinary tract infection NOS | 2 (2) | 0 (0)

N = number of patients in intent-to-treat population

n (%) = number and percentage of patients with reported adverse reaction

NOS = not otherwise specified

*The use of clindamycin may result in the overgrowth of non-susceptible fungal organisms in the vagina and may require antifungal treatment
Other reactions reported by <1% of those women treated with Clindesse include:
Dermatologic: Pruritic rash
Gastrointestinal: Diarrhea, vomiting
General: Fatigue
Immune System: Hypersensitivity
Nervous System: Dizziness
Reproductive System: Dysfunctional uterine bleeding, dysmennorrhea, intermenstrual bleeding, pelvic pain, vaginal burning, vaginal irritation, vulvar erythema, vulvitis, vulvovaginal discomfort, vulvovaginal dryness, vulvovaginitis

6.2 Other Clindamycin Formulations

Clindesse affords minimal peak serum levels and systemic exposure (AUCs) of clindamycin compared to an oral or intravenous dose of clindamycin [see Clinical Pharmacology (12.3)]. Data from well-controlled trials directly comparing clindamycin administered orally to clindamycin administered vaginally are not available.

The following additional adverse reactions and altered laboratory tests have been reported with the oral or parenteral use of clindamycin:

Gastrointestinal: Abdominal pain, esophagitis, nausea, Clostridioides difficile-associated diarrhea [see Warnings and Precautions (5.1)].

Hematopoietic: Transient neutropenia (leukopenia), eosinophilia, agranulocytosis, and thrombocytopenia have been reported. No direct etiologic relationship to concurrent clindamycin therapy could be made in any of these reports.

Hypersensitivity Reactions: Maculopapular rash, vesiculobullous rash, and urticaria have been observed during drug therapy. Generalized mild to moderate morbilliform-like skin rashes are the most frequently reported of all adverse reactions. Cases of erythema multiforme, some resembling Stevens-Johnson syndrome, have been associated with clindamycin. A few cases of anaphylactoid reactions have been reported.

Liver: Jaundice and abnormalities in liver function tests have been observed during clindamycin therapy.

Musculoskeletal: Cases of polyarthritis have been reported.

Renal: Although no direct relationship of clindamycin to renal damage has been established, renal dysfunction as evidenced by azotemia, oliguria, and/or proteinuria has been observed in rare instances.

Immune System: Drug reaction with eosinophilia and systemic symptoms (DRESS) cases have been reported.

6.3 Postmarketing Experience

The following adverse reactions have been identified during postapproval use of Clindesse. Because these reactions are reported voluntarily from a population of uncertain size, it is not always possible to reliably estimate their frequency or establish a causal relationship to drug exposure.

Dermatologic: Rash

Gastrointestinal: Hematochezia

Reproductive System: Vaginal erythema, vulvovaginal pruritis, vaginal discharge, vaginal swelling, vaginal bleeding, vaginal pain

7 DRUG INTERACTIONS

No formal drug interaction studies have been conducted for Clindesse.

7.1 Neuromuscular Blocking Agents

Orally or intravenously administered clindamycin has neuromuscular blocking properties that may enhance the action of other neuromuscular blocking agents. Therefore, it should be used with caution in patients receiving such agents.

8 USE IN SPECIFIC POPULATIONS

8.1 Pregnancy

Risk Summary

Clindesse has not been studied in pregnant women. The systemic exposure (based on AUC and Cmax) of Clindesse administered intravaginally is substantially lower than clindamycin administered intravenously [see Clinical Pharmacology (12.3)]; therefore, maternal use is not likely to result in significant fetal exposure to the drug. Available data from published observational studies and randomized controlled trials over decades of use with other clindamycin products during pregnancy have not identified an increased risk of major birth defects, miscarriage, or other adverse maternal and fetal outcomes.

In animal reproduction studies, no adverse developmental outcomes were observed in pregnant rats and mice administered oral doses of clindamycin at up to 600 mg/kg/day (58 and 29 times, respectively, the recommended human dose based on a body surface area comparison) (see Data).

The background risk of major birth defects and miscarriage for the indicated population is unknown. All pregnancies have a background risk of birth defect, loss or other adverse outcomes. In the U.S. general population, the estimated background risk of major birth defects and miscarriage in clinically recognized pregnancies is 2% to 4% and 15% to 20%, respectively.

Data

Animal Data

Reproduction studies have been performed in rats and mice using oral doses of clindamycin up to 600 mg/kg/day (58 and 29 times, respectively, the recommended human dose based on body surface area comparisons) and have revealed no evidence of harm to the fetus due to clindamycin.

8.2 Lactation

Risk Summary

The systemic exposure (based on AUC and Cmax) of Clindesse is substantially lower than intravenous administration of clindamycin [see Clinical Pharmacology (12.3)]; therefore, adverse effects on the breastfed infant are not expected from transfer of clindamycin into breastmilk. There are no data on the effect of clindamycin on milk production. The developmental and health benefits of breastfeeding should be considered along with the mother's clinical need for Clindesse and any potential adverse effects on the breastfed infant from Clindesse or from the underlying maternal condition.

8.3 Females and Males of Reproductive Potential

Contraception

Clindesse contains mineral oil that may weaken latex or rubber products such as condoms or vaginal contraceptive diaphragms. Therefore, the use of such barrier contraceptives is not recommended concurrently or for 5 days following treatment with Clindesse. During this time period, condoms may not be reliable for preventing pregnancy or for protecting against transmission of HIV and other sexually transmitted diseases [see Warnings and Precautions (5.2)].

8.4 Pediatric Use

The safety and efficacy of Clindesse in the treatment of bacterial vaginosis in post-menarchal females have been established on the extrapolation of clinical trial data from adult women. The safety and efficacy of Clindesse in pre-menarchal females have not been established.

8.5 Geriatric Use

Clinical studies with Clindesse did not include sufficient numbers of subjects 65 years of age or older to determine whether they respond differently than younger subjects. Other reported clinical experience has not identified differences in responses between the elderly and younger patients.

10 OVERDOSAGE

Vaginally applied clindamycin phosphate vaginal cream 2% could be absorbed in sufficient amounts to produce systemic effects [see Warnings and Precautions (5.1) and Adverse Reactions (6.2)].

11 DESCRIPTION

Clindamycin phosphate, a lincosamide, is a water soluble ester of the semi-synthetic antibiotic produced by a 7(S)-chloro-substitution of the 7(R)-hydroxyl group of the parent antibiotic lincomycin. The chemical name for clindamycin phosphate is methyl 7-chloro- 6,7,8-trideoxy-6-(1-methyl- trans- 4-propyl-L-2-pyrrolidinecarboxamido)-1-thio-L-threo-(alpha)-D-galacto-octopyranoside 2-(dihydrogen phosphate). It has a molecular weight of 504.96, and the molecular formula is C18H34CIN2O8PS. The structural formula is represented below:

Clindesse is a semi-solid, white cream, which contains clindamycin phosphate, USP, at a concentration equivalent to 20 mg clindamycin base per gram. The cream also contains edetate disodium, glycerol monoisostearate, lecithin, methylparaben, microcrystalline wax, mineral oil, polyglyceryl-3-oleate, propylparaben, purified water, silicon dioxide and sorbitol solution.

Clindesse does not comply with the pH test of the USP monograph for clindamycin phosphate vaginal cream.

12 CLINICAL PHARMACOLOGY

12.1 Mechanism of Action

Clindamycin is an antibacterial drug [see Clinical Pharmacology, Microbiology (12.4)].

12.3 Pharmacokinetics

Following a single intravaginal application of Clindesse cream to 20 healthy women, the mean (range) AUC0-inf and Cmax estimates were 175 (38.6 to 541) ng/mL•hr and 6.6 (0.8 to 39) ng/mL, respectively. The mean Cmax of clindamycin for Clindesse was approximately 0.3%, 0.1%, and 7.6% of that observed after the administration of a 150 mg Cleocin oral capsule (2.5 mcg/mL), a 600 mg Cleocin intravenous injection (10.9 mcg/mL), and a single dose of 100 mg of Cleocin Vaginal Cream (86.5 ng/mL), respectively. The peak serum concentration of clindamycin was attained approximately 20 hours post dosing for Clindesse.

12.4 Microbiology

Mechanism of Action

Clindamycin inhibits bacterial protein synthesis at the level of the bacterial ribosome. The antibiotic binds preferentially to the 50S ribosomal subunit and affects the process of peptide chain initiation. Although clindamycin phosphate is inactive in vitro, in vivo hydrolysis converts this compound to the antibacterially active clindamycin.

Activity In Vitro

Clindamycin is an antibacterial agent active in vitro against most strains of the following organisms that have been reported to be associated with bacterial vaginosis:

Bacteroides spp.

Gardnerella vaginalis

Mobiluncus spp.

Mycoplasma hominis

Peptostreptococcus spp.

Standard methodology for the susceptibility testing of the potential bacterial vaginosis pathogens has not been defined. Culture and sensitivity testing of bacteria are not routinely performed to establish the diagnosis of bacterial vaginosis [see Clinical Studies (14)].

13 NONCLINICAL TOXICOLOGY

13.1 Carcinogenesis, Mutagenesis, Impairment of Fertility

Long-term studies in animals have not been performed with clindamycin to evaluate carcinogenic potential. Genotoxicity tests performed included a rat micronucleus test and an Ames test. Both tests were negative. Fertility studies in rats treated orally with up to 300 mg/kg/day (29 times the recommended human dose based on body surface area comparisons) revealed no effects on fertility or mating ability.

14 CLINICAL STUDIES

Two clinical studies were conducted to evaluate the efficacy of Clindesse for the treatment of bacterial vaginosis. A clinical diagnosis of bacterial vaginosis was defined by the presence of a homogeneous vaginal discharge that (a) has a pH of greater than 4.5, (b) emits a “fishy” amine odor when mixed with a 10% KOH solution, and (c) contains clue cells on microscopic examination. Gram’s stain results consistent with a diagnosis of bacterial vaginosis include (a) markedly reduced or absent Lactobacillus morphology, (b) predominance of Gardnerella morphotype, and (c) absent or few white blood cells.

In a randomized, double-blind, placebo-controlled, clinical study involving 144 non-pregnant female patients aged 18 to 64 with a baseline Nugent score ≥4, Clindesse demonstrated statistically significantly higher cure rates over placebo as measured by therapeutic cure, clinical cure, and Nugent score cure (Table 2) assessed at 21-30 days after administration of the drug. Therapeutic cure was a composite endpoint which required both clinical cure and Nugent score cure. Clinical cure required normal vaginal discharge, vaginal pH < 4.7, < 20% clue cells on wet mount preparation, and negative “whiff” test (detection of amine odor on addition of 10% KOH solution to sample of the vaginal discharge). A Nugent score of 0-3 was considered a Nugent score cure. The Nugent scoring is based on microscopic examination of the Gram’s stained vaginal smears for quantification of specific bacterial morphotypes. Cure rates were consistently higher for Clindesse compared to placebo for the following demographic subsets: age, race, height, weight, sexual behavior, and recalcitrant infection status.

Table 2. Efficacy of Clindesse for Treatment of Bacterial Vaginosis in a Randomized, Double-Blind, Placebo-Controlled, Parallel Group Study

Outcome | Clindesse N=78 % Cure | Placebo N=66 % Cure | Treatment Difference† (%); [97.5% Confidence Interval]
Therapeutic Cure | 29.5 | 3.0 | 26.5 [14.0, 39.0]
Clinical Cure | 41.0 | 19.7 | 21.3 [4.7, 38.0]
Nugent Score Cure | 44.9 | 6.1 | 38.8 [24.6, 53.1]

N = number of patients in treatment group (modified intent-to-treat population defined as all subjects randomized who received at least one dose of study medication, and who had a baseline Nugent score of at least 4)

†Treatment difference = Clindesse minus placebo cure rates

In a second controlled clinical study involving 432 patients aged 18 to 78 with a baseline Nugent score of ≥4, 221 women self-administered a single dose of Clindesse, and 211 women self-administered a single daily dose of a formulation of clindamycin vaginal cream for 7 days. A single dose of Clindesse was shown to be similar to 7 daily doses of the clindamycin vaginal cream for treatment of bacterial vaginosis as measured by therapeutic cure, clinical cure or Nugent score cure assessed at 21-30 days after administration of the drug in the modified intent-to-treat population (Table 3) and for the per protocol population (Table 4). The study endpoints were identical to those described above for the placebo-controlled study. Statistical analyses did not reveal any significant differences when controlling for the following demographic variables: age, race, height, weight, sexual behavior, and recalcitrant infection status.

The cure rates reported in the clinical studies with Clindesse were based on resolution of 4 out of 4 Amsel criteria and a Nugent score of < 4, while the criteria for cure in previous clinical studies with the clindamycin vaginal cream were based solely on resolution of 2 out of 4 Amsel criteria, resulting in higher reported rates of cure for bacterial vaginosis.

Table 3. Efficacy of Clindesse in Treatment of Bacterial Vaginosis in a Randomized, Investigator-Blind, Active-Controlled Comparative Study – Modified-Intent-to-Treat

Outcome | Clindesse Single Dose N=221 % Cure | Clindamycin Vaginal Cream (7 doses) N=211 % Cure | Treatment Difference† (%) [95% Confidence Interval]
Therapeutic Cure | 33.0 | 37.0 | -3.9 [-12.9, 5.1]
Clinical Cure | 53.4 | 54.0 | -0.6 [-10.0, 8.8]
Nugent Score Cure | 45.7 | 49.3 | -3.6 [-13.1, 5.8]

†Treatment difference = Clindesse minus clindamycin vaginal cream cure rates

N = number of patients in treatment group (modified intent-to-treat population defined as all subjects randomized who received at least one dose of study medication, and who had a baseline Nugent score of at least 4)

Table 4. Efficacy of Clindesse in Treatment of Bacterial Vaginosis in a Randomized, Investigator-Blind, Active-Controlled Comparative Study – Per Protocol

Outcome | Clindesse Single Dose N=126 % Cure | Clindamycin Vaginal Cream (7 doses) N=125 % Cure | Treatment Difference† (%) [95% Confidence Interval]
Therapeutic Cure | 42.1 | 45.6 | -3.5 [-15.8, 8.7]
Clinical Cure | 64.3 | 63.2 | 1.1 [-10.8, 13.0]
Nugent Score Cure | 56.5‡ | 57.7‡ | -1.3 [-13.6, 11.1]

†Treatment difference = Clindesse minus clindamycin vaginal cream cure rates

N = number of patients in treatment group (per protocol population defined as all subjects included in the modified intent-to-treat population who completed the study without significant protocol violation)

‡Four subjects (2 from each treatment group) did not have complete Nugent scores and were not included in the Nugent Score cure analysis

16 HOW SUPPLIED/STORAGE AND HANDLING

Clindesse (clindamycin phosphate) Vaginal Cream, 2%, is available in cartons containing one single-dose, pre-filled disposable applicator (NDC 45802-042-01). Each applicator delivers approximately 5 g of vaginal cream containing approximately 100 mg of clindamycin.

Store at 20°-25°C (68°-77°F). [See USP Controlled Room Temperature.]

Avoid heat above 30°C (86°F).

17 PATIENT COUNSELING INFORMATION

Vaginal Intercourse and Use with Vaginal Products

Instruct the patient not to engage in vaginal intercourse, or use other vaginal products (such as tampons or douches) during treatment with this product.

Use with Condoms and Vaginal Contraceptive Diaphragms

Advise the patient that Clindesse contains mineral oil that may weaken latex or rubber products such as condoms or vaginal contraceptive diaphragms. Therefore, do not use barrier contraceptives concurrently or for 5 days following treatment with Clindesse. During this time period, condoms may not be reliable for preventing pregnancy or for protecting against transmission of HIV and other sexually transmitted diseases [see Warnings and Precautions (5.2) and Use in Specific Populations (8.3)].

Fungal Vaginal Infections

Inform the patient that vaginal fungal infections can occur following use of Clindesse and may require treatment with an antifungal drug [see Adverse Reactions (6.1)].

Accidental Exposure to the Eye

Inform the patient that Clindesse contains ingredients which cause burning and irritation of the eye. In the event of accidental contact with the eye, rinse the eye with copious amounts of cool tap water and consult a physician.

Manufactured by Padagis®
Yeruham, Israel

Patents at www.padagis.com/patents

Cleocin is a registered trademark of Pharmacia & Upjohn Company.

2S000 RC PH7

Patient Information

Clindesse (clin-DESS)

(clindamycin phosphate)

Vaginal Cream, 2%

Important Information: Clindesse is for intravaginal use only. Do not use in the eyes, mouth, or on your skin.

What is Clindesse?

• Clindesse vaginal cream is a prescription medicine used to treat bacterial vaginal infections in women who are not pregnant.

• It is not known if Clindesse is safe and effective in females who have not yet reached puberty.

Do not use Clindesse if you:

• are allergic to clindamycin or other lincosamide antibiotic medicines or are allergic to any of the ingredients in Clindesse. See the end of this leaflet for a complete list of ingredients in Clindesse.

• have had bowel problems such as:

◦ inflammation of your intestines (enteritis)

◦ inflammation of your colon (colitis)

◦ diarrhea due to a Clostridioides difficile-associated diarrhea (CDAD)

Before using Clindesse, tell your healthcare provider about all of your medical conditions, including if you:

• are pregnant or plan to become pregnant. It is not known if Clindesse will harm your unborn baby. Tell your healthcare provider if you become pregnant during treatment with Clindesse.

• are breastfeeding or plan to breastfeed. The amount of Clindesse which passes into your breast milk is low and is not expected to harm your baby. Talk with your healthcare provider about the best way to feed your baby while using Clindesse.

Tell your healthcare provider about all the medicines you take, including prescription and over-the-counter medicines, vitamins, and herbal supplements.

How should I use Clindesse?

• Use Clindesse exactly as your healthcare provider tells you to use it.

• Use 1 filled applicator of Clindesse in the vagina at any time of the day.

• Do not use any medicine from the tube or applicator more than 1 time. Clindesse is for 1 time (single-use) only.

• Do not use Clindesse in the eyes, mouth, or on your skin. If you accidently get Clindesse in your eyes rinse your eyes with cool tap water right away and call your healthcare provider.

• See the Instructions for Use at the end of this Patient Information leaflet for more information about how to fill the applicator and use Clindesse.

What should I avoid while using Clindesse?

After you insert Clindesse:

• Do not have vaginal sex or use vaginal products (such as tampons or douches) during your treatment.

• Do not use barrier contraceptive products during your treatment or for 5 days after your treatment.

◦ Barrier contraceptives include condoms or contraceptive diaphragms used for birth control or to protect yourself against Human Immunodeficiency Virus (HIV) or other sexually transmitted diseases (STDs).

◦ Clindesse contains mineral oil that may weaken latex or rubber products in condoms or vaginal contraceptive diaphragms.

◦ Condoms or vaginal contraceptive diaphragms may not work as well for preventing pregnancy, or for protecting against HIV and other STDs.

What are the possible side effects of Clindesse?

Clindesse may cause serious side effects, including diarrhea. One type of diarrhea is caused by an infection in your intestines called Clostridioides difficile-associated diarrhea (CDAD), which may range in severity from mild diarrhea to colitis that can lead to death. If you have diarrhea after you use Clindesse, call your healthcare provider.

The most common side effects of Clindesse include:

• fungal infection in your vagina that may require treatment with an antifungal medicine.

• headache

• back pain

• constipation

• urinary tract infection

Tell your healthcare provider if you have any side effect that bothers you or that does not go away.

These are not all of the possible side effects of Clindesse. For more information, ask your healthcare provider or pharmacist.

Call your doctor for medical advice about side effects. You may report side effects to FDA at 1-800-FDA-1088.

How should I store Clindesse?

• Store Clindesse between 68°F to 77°F (20°C to 25°C).

Keep Clindesse and all medicines out of the reach of children.

General information about the safe and effective use of Clindesse.

Medicines are sometimes prescribed for purposes other than those listed in a patient information leaflet. Do not use Clindesse for a condition for which it was not prescribed. Do not give Clindesse to other people, even if they have the same symptoms you have. It may harm them.

You can ask your pharmacist or healthcare provider for information about Clindesse that is written for health professionals.

What are the ingredients in Clindesse?

Active ingredient: clindamycin phosphate

Inactive ingredients: edetate disodium, glycerol monoisostearate, lecithin, methylparaben, microcrystalline wax, mineral oil, polyglyceryl-3-oleate, propylparaben, purified water, silicon dioxide and sorbitol solution.

For more information, go to www.clindesse.com or call 1-866-634-9120

This Patient Information has been approved by the U.S. Food and Drug Administration

01/2025

Instructions for Use

Clindesse (clin-DESS)

(clindamycin phosphate)

Vaginal Cream, 2%

For vaginal use only.

Do not put Clindesse in your eyes, mouth, or on your skin.

It is important that you read and follow these directions on how to use Clindesse vaginal cream properly.

Clindesse comes in a single-dose, pre-filled, disposable applicator that gives you a certain amount of clindamycin cream to be inserted into your vagina.

Step 1. Prepare the applicator.

Peel back the protective foil and remove the pre-filled applicator. Do not remove the tip.

The applicator is made to be used with the tip in place.

Do not use the applicator if the tip has been removed (see Figure 1).

Activate the plunger before you use it. To activate the plunger, pull the ring back to fully extend the plunger while you firmly hold the applicator (see Figure 2).

Step 2. Insert the applicator.

Gently insert the applicator into your vagina as far as it will comfortably go (see Figure 3).

Step 3. Apply the cream.

Push the plunger in until all of the cream goes into your vagina (see Figures 4 and 5).

Step 4. Remove the empty applicator from your vagina and throw it away in the trash.

This Instructions for Use has been approved by the U.S. Food and Drug Administration

01/2025

Package/Label Display Panel - Carton

Clindesse®

(clindamycin phosphate) Vaginal Cream, 2%

NDC 45802-042-01

Rx Only

This applicator delivers approximately 5 g of vaginal cream containing approximately 100 mg of clindamycin.

One complete course of therapy in a convenient, prefilled, and disposable applicator.

NET WT 5.8 g